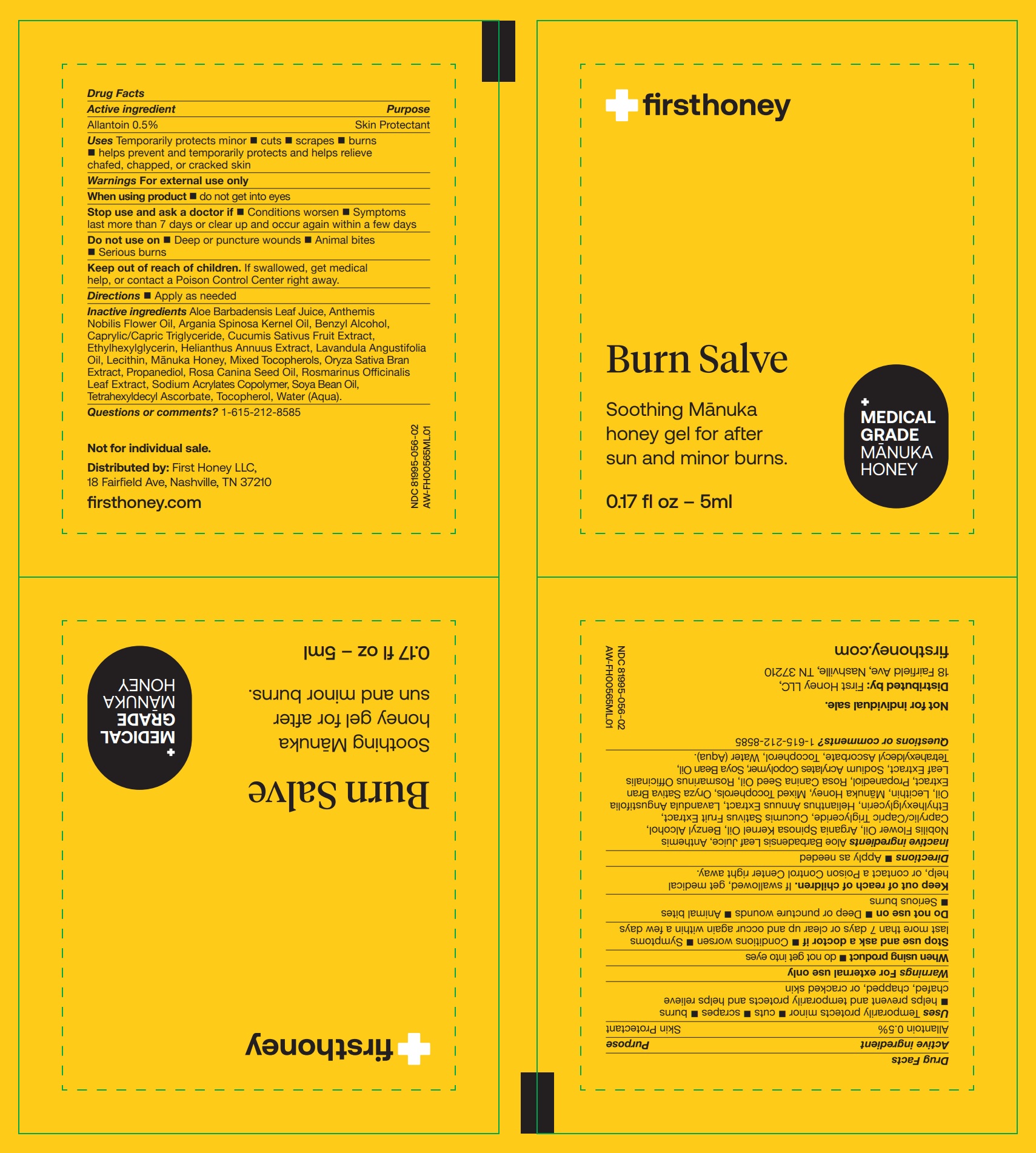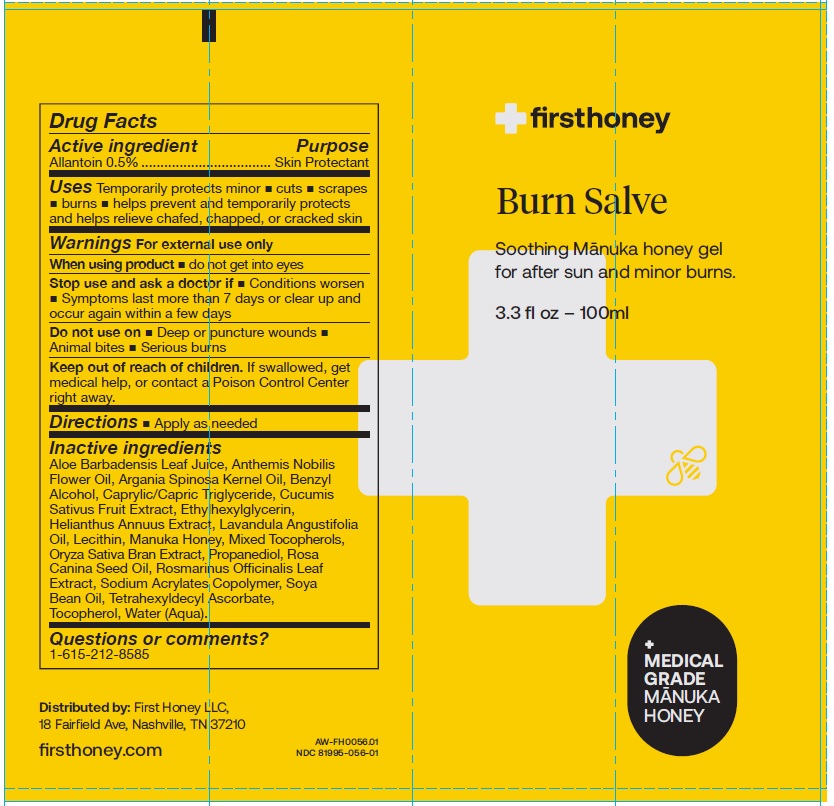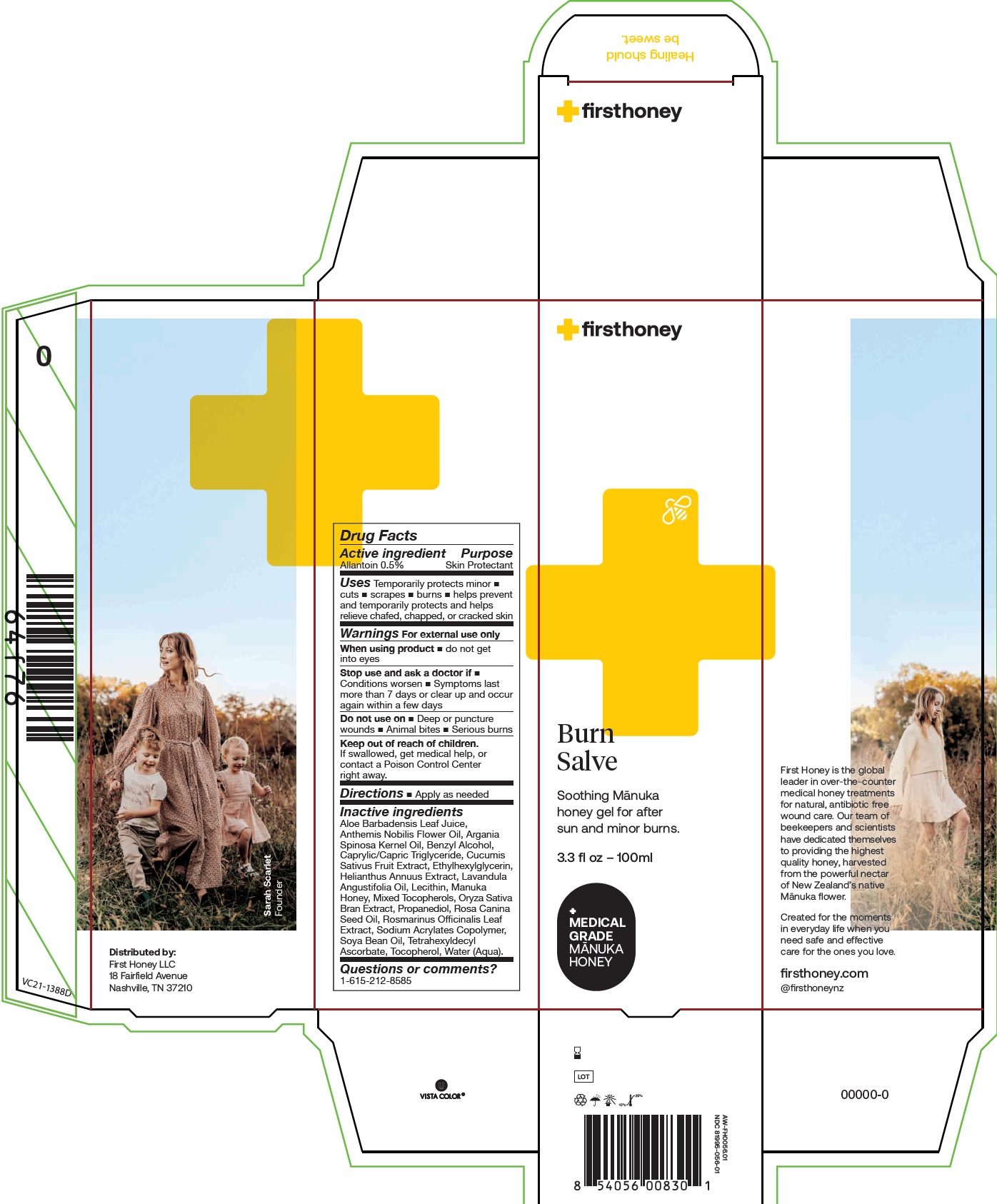 DRUG LABEL: First honey Burn Salve
NDC: 81995-056 | Form: CREAM
Manufacturer: First Honey, LLC
Category: otc | Type: HUMAN OTC DRUG LABEL
Date: 20250204

ACTIVE INGREDIENTS: ALLANTOIN 5 mg/1 mL
INACTIVE INGREDIENTS: ALOE VERA LEAF; CHAMAEMELUM NOBILE FLOWER OIL; ARGAN OIL; BENZYL ALCOHOL; MEDIUM-CHAIN TRIGLYCERIDES; ETHYLHEXYLGLYCERIN; LAVENDER OIL; HONEY; TOCOPHEROL; PROPANEDIOL; ROSA CANINA SEED OIL; ROSEMARY; HYDROGENATED SOYBEAN OIL; TETRAHEXYLDECYL ASCORBATE; WATER

First honey Burn Salve

Active ingredient

Allantoin 0.5%

Purpose

Skin Protectant

Uses

- Temporarily protects minor
- cuts
- scrapes
- burns
- helps prevent and temporarily protects and helps relieve chafed, chapped, or cracked skin

Warnings

For external use only

When using product

- do not get into eyes

Stop use and ask a doctor if

- Conditions worsen
- Symptoms last more than 7 days or clear up and occur again within a few days

Do not use on

- Deep or puncture
- wounds
- Animal bites
- Serious burns

Keep out of reach of children.

If swallowed, get medical help, or contact a Poison Control Center right away.

Directions

- Apply as needed

Inactive ingredients

Aloe Barbadensis Leaf Juice, Anthemis Nobilis Flower Oil, Argania Spinosa Kernel Oil, Benzyl Alcohol, Caprylic/Capric Triglyceride, Cucumis Sativus Fruit Extract, Ethylhexylglycerin, Helianthus Annuus Extract, Lavandula Angustifolia Oil, Lecithin, Manuka Honey, Mixed Tocopherols, Oryza Sativa Bran Extract, Propanediol, Rosa Canina Seed Oil, Rosmarinus Officinalis Leaf Extract, Sodium Acrylates Copolymer, Soya Bean Oil, Tetrahexyldecyl Ascorbate, Tocopherol, Water (Aqua).

Questions or comments?

1-615-212-8585